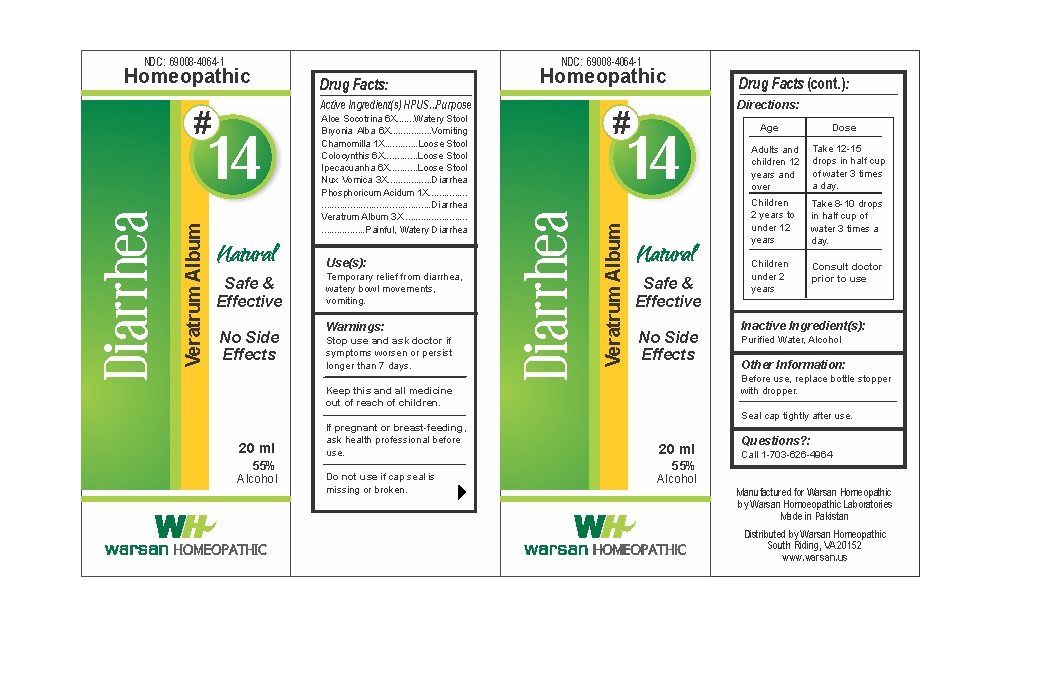 DRUG LABEL: Combination Remedy 14 - Diarrhea
NDC: 69008-4064 | Form: SOLUTION/ DROPS
Manufacturer: Warsan Homoeopathic Laboratories
Category: homeopathic | Type: HUMAN OTC DRUG LABEL
Date: 20171225

ACTIVE INGREDIENTS: MATRICARIA RECUTITA 1 [hp_X]/1 mL; CITRULLUS COLOCYNTHIS FRUIT PULP 6 [hp_X]/1 mL; ALOE VERA LEAF 6 [hp_X]/1 mL; STRYCHNOS NUX-VOMICA SEED 3 [hp_X]/1 mL; PHOSPHORIC ACID 1 [hp_X]/1 mL; BRYONIA ALBA ROOT 6 [hp_X]/1 mL; IPECAC 6 [hp_X]/1 mL; VERATRUM ALBUM ROOT 3 [hp_X]/1 mL
INACTIVE INGREDIENTS: ALCOHOL; WATER

Stop use and ask doctor if symptoms worsen or persist longer than 7 days.

If pregnant or breast-feeding, ask health professional before use.

Do not use if tamper evident seal is missing or broken.

Keep out of reach of children.

ACTIVE INGREDIENT

Aloe Socotrina 6X

Bryonia Alba 6X

Chamomilla 1X

Colocynthis 6X

Ipecacuanha 6X

Nux Vomica 3X

Phosphoricum Acidum 1X

Veratrum Album 3X

PURPOSE

Temporary relief from diarrhea, watery bowl movements, vomiting.

INACTIVE INGREDIENT

Purified Water

Alcohol

DOSAGE AND ADMINISTRATION

Adults and children 12 years and older: Take 10-15 drops in half cup of water 3 times a day.

Children 2 years to under 12 years: Take 8-10 drops in half cup of water of 3 times a day.

Children under 2 years: Consult doctor prior to use.

INDICATIONS AND USAGE

Temporary relief from diarrhea, watery bowl movements, vomiting.